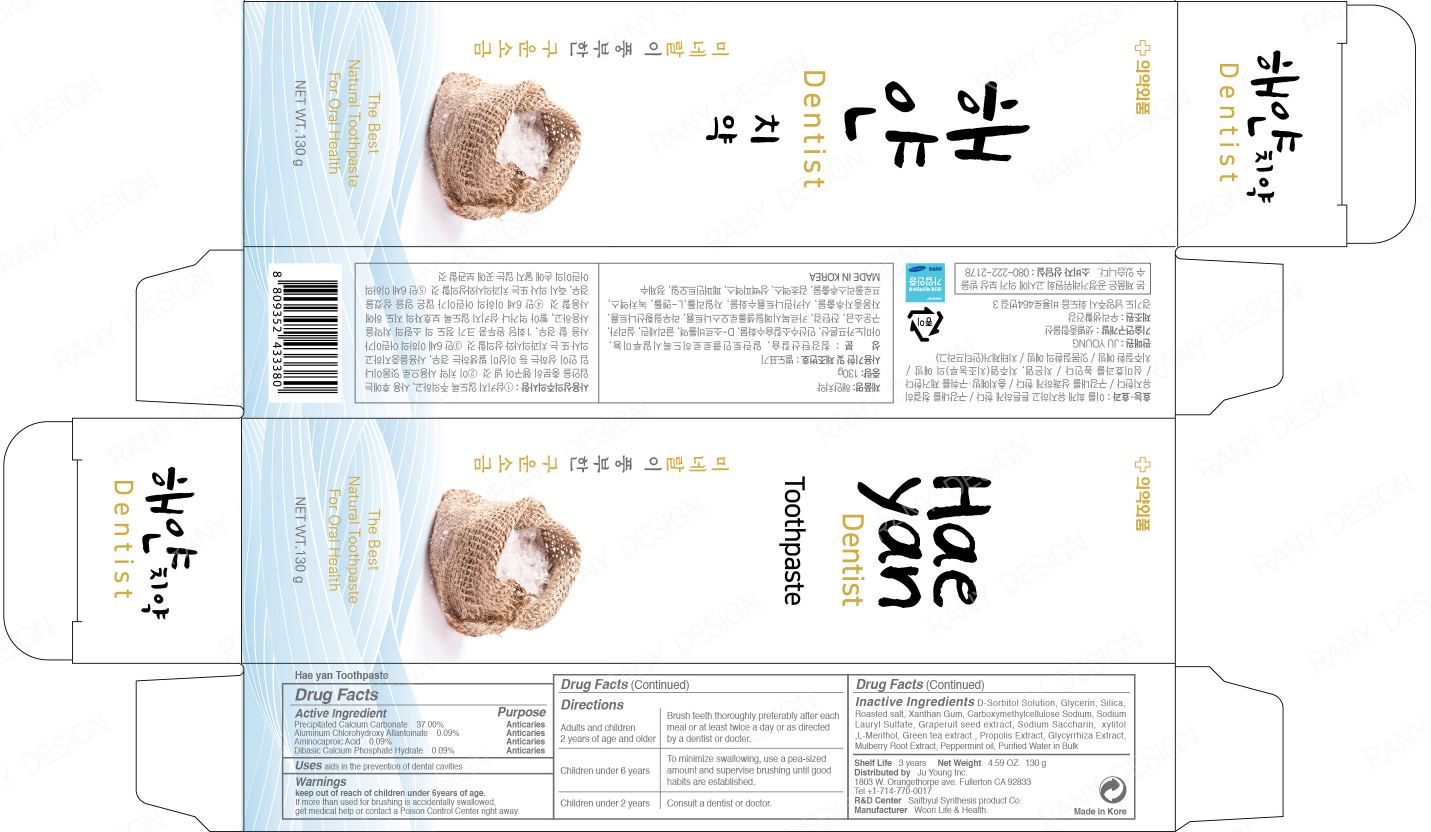 DRUG LABEL: Hae Yan Tooth
NDC: 73065-0004 | Form: PASTE
Manufacturer: WOORILIFE&HEALTH
Category: otc | Type: HUMAN OTC DRUG LABEL
Date: 20200529

ACTIVE INGREDIENTS: AMINOCAPROIC ACID 0.09 g/100 g; DIBASIC CALCIUM PHOSPHATE DIHYDRATE 0.09 g/100 g; CALCIUM CARBONATE 37 g/100 g; ALCLOXA 0.09 g/100 g
INACTIVE INGREDIENTS: XYLITOL; LEVOMENTHOL

Woorilife&Health - Hae Yan Toothpaste

ACTIVE INGREDIENT

precipitated calcium carbonate, aminocaproic acid, aluminium chlorohydrin allantoinate, dibasic calcium phosphate hydrate

INACTIVE INGREDIENT

d-sorbitol solution, glycerin, silica, roasted salt, xanthan gum, carboxymethylcellulose sodium, sodium lauryl sulfate, grapefruit seed extract, sodium saccharin, xylitol, l-menthol, green tea extract, propolis extract, glycyrrhiza extract, mulberry root extract, peppermint oil, purified water

PURPOSE

aids in the prevention of dental cavities.

keep out of reach of the children

INDICATIONS AND USAGE

- Adults and children 2 years of age and older

Brush teeth thoroughly preferably after each meal or at least twice a day or as directed by a dentist or docter.

- Children under 6 years

To minimize swallowing, use a pea-sized amount and supervise brushing until good habits are established.

- Children under 2 years

Consult a dentist or doctor

WARNINGS

1) Be careful not to swallow it, and rinse your mouth thoroughly after use.

2) If any abnormalities such as gum or mouth damage are caused by using this toothpaste, stop using the product and consult a doctor or dentist.

3) For children under 6 years of age, use a small amount of pea toothpaste per serving and use it under the supervision of a guardian to avoid sucking or swallowing.

4) If a child under 6 years of age swallows a large amount, consult a doctor or dentist immediately.

5) Keep out of reach of children under 6 years old.

DOSAGE AND ADMINISTRATION

for external use only